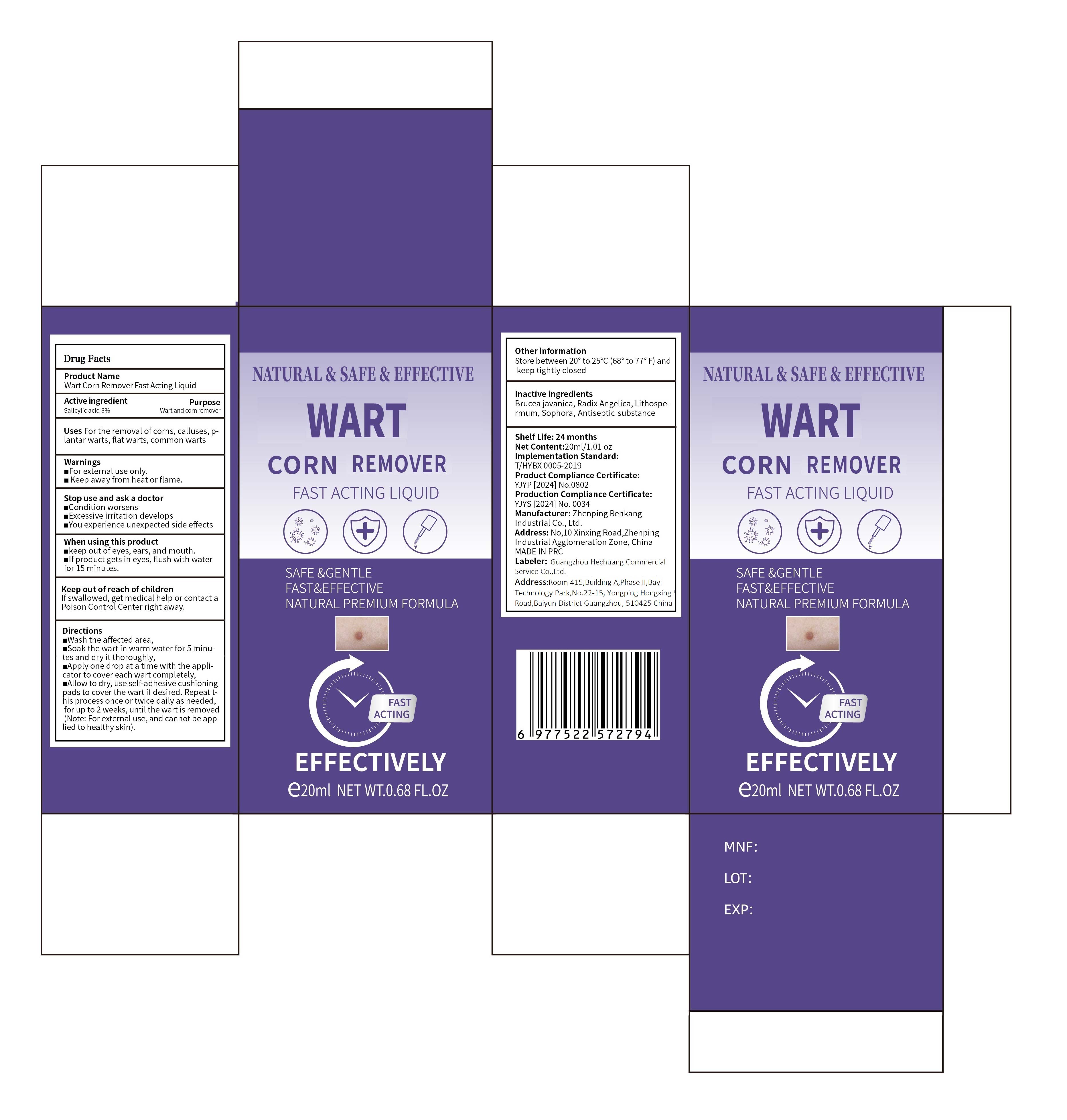 DRUG LABEL: Wart Corn Remover Fast Acting Liquid
NDC: 87298-010 | Form: LIQUID
Manufacturer: Guangzhou Hechuang Commercial Service Co.,Ltd.
Category: otc | Type: HUMAN OTC DRUG LABEL
Date: 20251223

ACTIVE INGREDIENTS: SALICYLIC ACID 8 g/100 g
INACTIVE INGREDIENTS: BRUCEA JAVANICA WHOLE; SOPHORA FLAVESCENS ROOT; ALCOHOL; LITHOSPERMUM INCISUM WHOLE; ANGELICA DAHURICA VAR. FORMOSANA WHOLE

Active Ingredients

Salicylic acid 8%

Purpose:Wart and corn remover

Purpose

Wart and corn remover

Inactive Ingredients

BRUCEA JAVANICA WHOLE、
SOPHORA FLAVESCENS ROOT、
ALCOHOL、
LITHOSPERMUM INCISUM WHOLE、
ANGELICA DAHURICA VAR. FORMOSANA WHOLE

Uses

Uses For the removal of corns, calluses, plantar warts, flat warts, common warts

Directions

■Wash the affected area,
■Soak the wart in warm water for 5 minutes and dry it thoroughly,
■Apply one drop at a time with the applicator to cover each wart completely,
■Allow to dry, use self-adhesive cushioning pads to cover the wart if desired. Repeat this process once or twice daily as needed, for up to 2 weeks, until the wart is removed (Note: For external use, and cannot be applied to healthy skin).

When using this product

Keep out of eyes,ears,and mouth.
If product gets in eyes,flush with water for 15 minutes.

Stop use and ask a doctor

Condition worsens
Excessive irritation develops
You experience unexpected side effects

Keep out of reach of children

If swallowed,get medical help or contact a plison control center right away.

Warnings

For external use only.
keep away from heat or flame.

Other information

Store between 20° to 25℃(68° to 77°F) and keep tightly closed